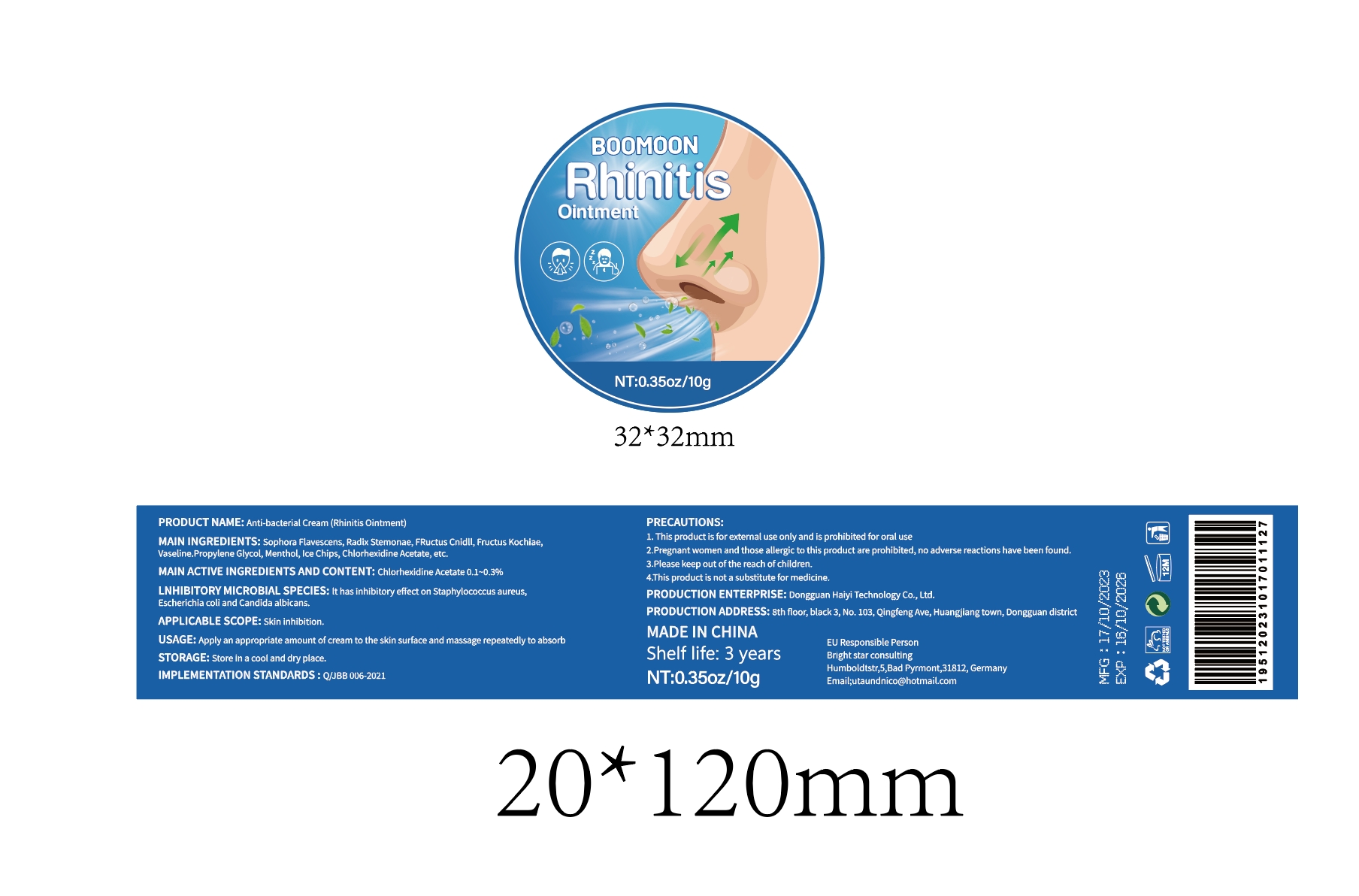 DRUG LABEL: Anti-bacterial Cream (Rhinitis Ointment)
NDC: 84732-022 | Form: CREAM
Manufacturer: Dongguan Haiyi Technology Co.,Ltd.
Category: otc | Type: HUMAN OTC DRUG LABEL
Date: 20240928

ACTIVE INGREDIENTS: SOPHORA FLAVESCENS WHOLE 1 mg/10 g; MENTHOL 1 mg/10 g
INACTIVE INGREDIENTS: CHLORHEXIDINE ACETATE; PROPYLENE GLYCOL

ACTIVE INGREDIENT

Sophora Flavescens
Radix Stemonae
Fructus Cnidii
Fructus Kochiae Menthol
Chlorhexidine Acetate

Inactive ingredient

Vaseline
Propylene Glycol
Ice Chips

Purpose section

it has inhibitory effect on Staphylococcus aureus,Escherichia coli and Candida albicans.

Warning

1. This product is for extemal use only and is prohibited for oral use

2.Pregnant women and those allergic to this product are prohibited, no adverse reactions have been found.

3.Please keep out of the reach of children.
4.This product is not a substitute for medicine.

stop use

This product may cause allergic reactions in asmall number of people.
lf youexperience any discomfort,please stop using it immediately.

not use

Not suitable for use by children, pregnantor breastfeeding people.

OUT OF CHILDREN

KEEP THE PRODUCT OUT OF REACH OF CHILDREN to

HOW TO USE

Apply an appropriate amount of cream to the skin surface and massage repeatedly to absorb

Dosage

take an appropriateamount,Use 2-3 times a week